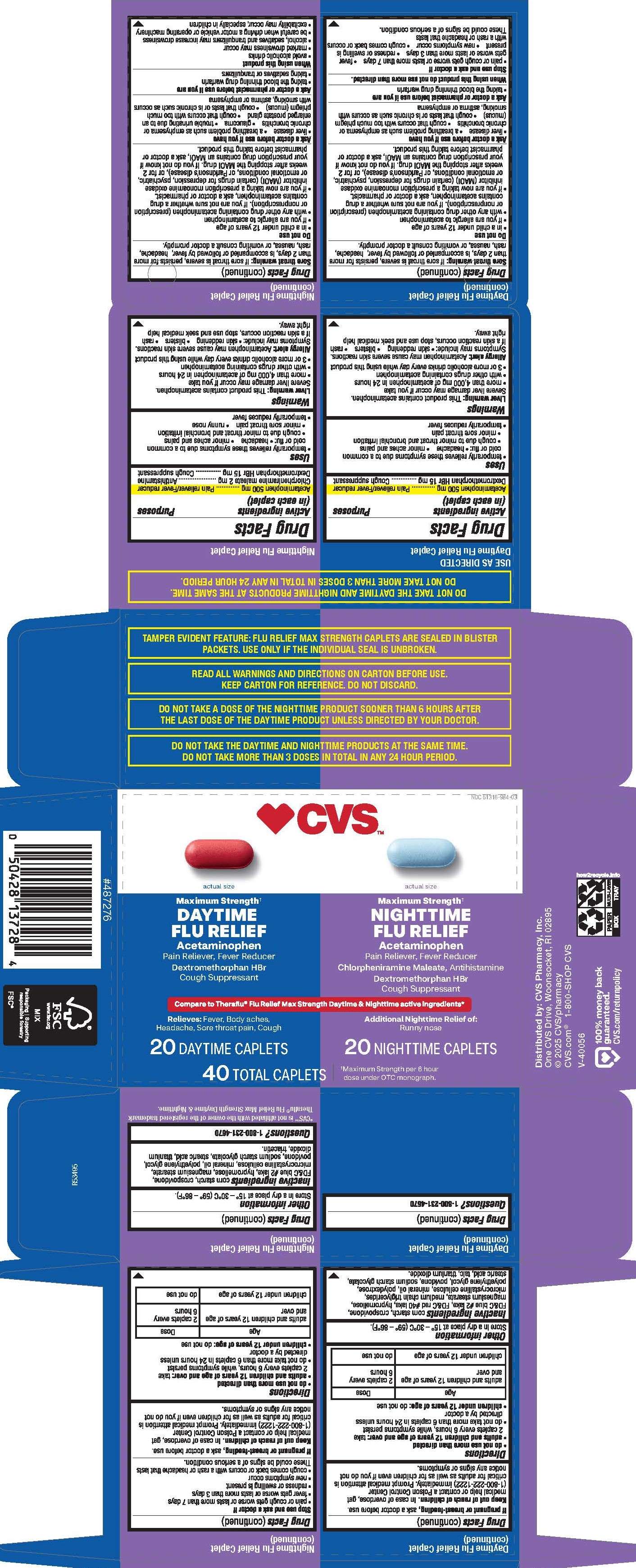 DRUG LABEL: Acetaminophen, Chlorpheniramine Maleate, Dextromethorphan HBr
NDC: 51316-984 | Form: KIT | Route: ORAL
Manufacturer: CVS Pharmacy, Inc
Category: otc | Type: HUMAN OTC DRUG LABEL
Date: 20250904

ACTIVE INGREDIENTS: DEXTROMETHORPHAN HYDROBROMIDE 15 mg/1 1; ACETAMINOPHEN 500 mg/1 1; CHLORPHENIRAMINE MALEATE 2 mg/1 1; DEXTROMETHORPHAN HYDROBROMIDE 15 mg/1 1; ACETAMINOPHEN 500 mg/1 1
INACTIVE INGREDIENTS: CROSPOVIDONE; POLYETHYLENE GLYCOL, UNSPECIFIED; FD&C BLUE NO. 2 ALUMINUM LAKE; HYPROMELLOSES; MAGNESIUM STEARATE; POVIDONE; SODIUM STARCH GLYCOLATE TYPE A; STEARIC ACID; STARCH, CORN; TITANIUM DIOXIDE; MICROCRYSTALLINE CELLULOSE; TRIACETIN; MINERAL OIL; TITANIUM DIOXIDE; FD&C BLUE NO. 2 ALUMINUM LAKE; STEARIC ACID; POVIDONE; CROSPOVIDONE; MEDIUM-CHAIN TRIGLYCERIDES; STARCH, CORN; TALC; MAGNESIUM STEARATE; MICROCRYSTALLINE CELLULOSE; POLYDEXTROSE; SODIUM STARCH GLYCOLATE TYPE A; FD&C RED NO. 40 ALUMINUM LAKE; MINERAL OIL; HYPROMELLOSES; POLYETHYLENE GLYCOL, UNSPECIFIED

6044-CVS

Daytime Flu Relief Maximum Strength

Drug Facts

Active ingredients (in each caplet)

Acetaminophen 500 mg

Dextromethorphan HBr 15 mg

Purposes

Pain reliever/Fever reducer

Cough suppressant

Uses

- temporarily relieves these symptoms due to a common cold or flu:
  - headache
  - minor aches and pains
  - cough due to minor throat and bronchial irritation
  - minor sore throat pain
- temporarily reduces fever

WARNINGS

Liver warning: This product contains acetaminophen. Severe liver damage may occur if you take

- more than 4,000 mg of acetaminophen in 24 hours
- with other drugs containing acetaminophen
- 3 or more alcoholic drinks every day while using this product

Allergy alert: Acetaminophen may cause severe skin reactions.

Symptoms may include: • skin reddening • blisters • rash

If a skin reaction occurs, stop use and seek medical help right away.

Sore throat warning: If sore throat is severe, persists for more than 2 days, is accompanied or followed by fever, headache, rash, nausea, or vomiting consult a doctor promptly.

DO NOT USE

- in a child under 12 years of age
- if you are allergic to acetaminophen
- with any other drug containing acetaminophen (prescription or nonprescription). If you are not sure whether a drug contains acetaminophen, ask a doctor or pharmacist.
- if you are now taking a prescription monoamine oxidase inhibitor (MAOI) (certain drugs for depression, psychiatric, or emotional conditions, or Parkinson's disease) or for 2 weeks after stopping the MAOI drug. If you do not know if your prescription drug contains an MAOI, ask a doctor or pharmacist before taking this product.

ASK DOCTOR

- liver disease
- a breathing problem such as emphysema or chronic bronchitis
- cough that occurs with too much phlegm (mucus)
- cough that lasts or is chronic such as occurs with smoking, asthma or emphysema

ASK DOCTOR/PHARMACIST

- taking the blood thinning drug warfarin

When using this product do not use more than directed.

STOP USE

- pain or cough gets worse or lasts more than 7 days
- fever gets worse or lasts more than 3 days
- redness or swelling is present
- new symptoms occur
- cough comes back or occurs with a rash or headache that lasts

These could be signs of a serious condition.

PREGNANCY OR BREAST FEEDING

If pregnant or breast-feeding, ask a doctor before use.

Keep out of reach of children.

OVERDOSAGE

In case of overdose, get medical help or contact a Poison Control Center (1-800-222-1222) immediately. Prompt medical attention is critical for adults as well as for children even if you do not notice any signs or symptoms.

Directions

- do not use more than directed
- adults and children 12 years of age and over: take 2 caplets every 6 hours, while symptoms persist
- do not take more than 6 caplets in 24 hours unless directed by a doctor
- children under 12 years of age: do not use
  Age | Dose
  adults and children 12 years of age and over | 2 caplets every 6 hours
  children under 12 years of age | do not use

Other information

Store in a dry place at 15º - 30°C (59° -86°F).

INACTIVE INGREDIENT

corn starch, crospovidone, FD&C blue #2 lake, FD&C red #40 lake, hypromellose, magnesium stearate, medium chain triglycerides,
microcrystalline cellulose, mineral oil, polydextrose, polyethylene glycol, povidone, sodium starch glycolate, stearic acid, talc, titanium dioxide.

QUESTIONS

1-800-231-4670

Nighttime Flu Relief Maximum Strength

Drug facts

Active ingredients (in each caplet)

Acetaminophen 500 mg

Chlorpheniramine maleate 2 mg

Dextromethorphan HBr 15 mg

Purposes

Pain reliever/Fever reducer

Antihistamine

Cough suppressant

Uses

- temporarily relieves these symptoms due to a common cold or flu:
- headache
- minor aches and pains
- cough due to minor throat and bronchial irritation
- minor sore throat pain
- runny nose
- temporarily reduces fever

WARNINGS

Liver warning: This product contains acetaminophen. Severe liver damage may occur if you take

- more than 4,000 mg of acetaminophen in 24 hours
- with other drugs containing acetaminophen
- 3 or more alcoholic drinks every day while using this product

Allergy alert: Acetaminophen may cause severe skin reactions.

Symptoms may include: • skin reddening • blisters • rash

If a skin reaction occurs, stop use and seek medical help right away.

Sore throat warning: If sore throat is severe, persists for more than 2 days, is accompanied or followed by fever, headache, rash, nausea, or vomiting consult a doctor promptly.

DO NOT USE

- in a child under 12 years of age
- if you are allergic to acetaminophen
- with any other drug containing acetaminophen (prescription or nonprescription). If you are not sure whether a drug contains acetaminophen, ask a doctor or pharmacist.
- if you are now taking a prescription monoamine oxidase inhibitor (MAOI) (certain drugs for depression, psychiatric, or emotional conditions, or Parkinson's disease) or for 2 weeks after stopping the MAOI drug. If you do not know if your prescription drug contains an MAOI, ask a doctor or pharmacist before taking this product.

ASK DOCTOR

- liver disease
- a breathing problem such as emphysema or chronic bronchitis
- glaucoma
- trouble urinating due to an enlarged prostate gland
- cough that occurs with too much phlegm (mucus)
- cough that lasts or is chronic such as occurs with smoking, asthma or emphysema

ASK DOCTOR/PHARMACIST

- taking the blood thinning drug warfarin
- taking sedatives or tranquilizers

WHEN USING

- avoid alcoholic drinks
- marked drowsiness may occur
- alcohol, sedatives and tranquilizers may increase drowsiness
- be careful when driving a motor vehicle or operating machinery
- excitability may occur, especially in children

STOP USE

- pain or cough gets worse or lasts more than 7 days
- fever gets worse or lasts more than 3 days
- redness or swelling is present
- new symptoms occur
- cough comes back or occurs with a rash or headache that lasts

These could be signs of a serious condition.

PREGNANCY OR BREAST FEEDING

If pregnant or breast-feeding, ask a doctor before use.

Keep out of reach of children.

OVERDOSAGE

In case of overdose, get medical help or contact a Poison Control Center (1-800-222-1222) immediately. Prompt medical attention is critical for adults as well as for children even if you do not notice any signs or symptoms.

Directions

- do not use more than directed
- adults and children 12 years of age and over: take 2 caplets every 6 hours, while symptoms persist
- do not take more than 6 caplets in 24 hours unless directed by a doctor
- children under 12 years of age: do not use

Age | Dose
adults and children 12 years of age and over | 2 caplets every 6 hours
children under 12 years of age | do not use

Other information

Store in a dry place at 15° – 30°C (59° – 86°F).

INACTIVE INGREDIENT

corn starch, crospovidone, FD&C blue #2 lake, hypromellose, magnesium stearate, microcrystalline cellulose, mineral oil, polyethylene glycol, povidone, sodium starch glycolate, stearic acid, titanium dioxide, triacetin.

QUESTIONS

1-800-231-4670

*CVS™ is not affiliated with the owner of the registered trademark Theraflu® Flu Relief Max Strength Daytime & Nighttime.

Distributed by: CVS Pharmacy, Inc.
One CVS Drive, Woonsocket, RI 02895
© 2025 CVS/pharmacy
CVS.com® 1-800-SHOP CVS

TAMPER EVIDENT FEATURE: FLU RELIEF MAX STRENGTH CAPLETS ARE SEALED IN BLISTER PACKETS. USE ONLY IF THE INDIVIDUAL SEAL IS UNBROKEN.

READ ALL WARNINGS AND DIRECTIONS ON CARTON BEFORE USE.
KEEP CARTON FOR REFERENCE. DO NOT DISCARD.

DO NOT TAKE A DOSE OF THE NIGHTTIME PRODUCT SOONER THAN 6 HOURS AFTER
THE LAST DOSE OF THE DAYTIME PRODUCT UNLESS DIRECTED BY YOUR DOCTOR.

DO NOT TAKE THE DAYTIME AND NIGHTTIME PRODUCTS AT THE SAME TIME.
DO NOT TAKE MORE THAN 3 DOSES IN TOTAL IN ANY 24 HOUR PERIOD.

PACKAGE LABEL

CVS™

NDC 51316-984-03

Compare to Theraflu® Flu Relief Max Strength Daytime & Nighttime active ingredients*

Maximum Strength†

DAYTIME FLU RELIEF

Acetaminophen

Pain Reliever, Fever Reducer

Dextromethorphan HBr

Cough Suppressant

Relieves: Fever, Body aches, Headache, Sore throat pain, Cough

20 DAYTIME CAPLETS

Maximum Strength†

NIGHTTIME FLU RELIEF

Acetaminophen

Pain Reliever, Fever Reducer

Chlorpheniramine Maleate,

Antihistamine

Dextromethorphan HBr

Cough Suppressant

Additional Nighttime Relief of: Runny nose

20 NIGHTTIME CAPLETS

40 TOTAL CAPLETS

†Maximum Strength per 6 hour dose under OTC monograph.